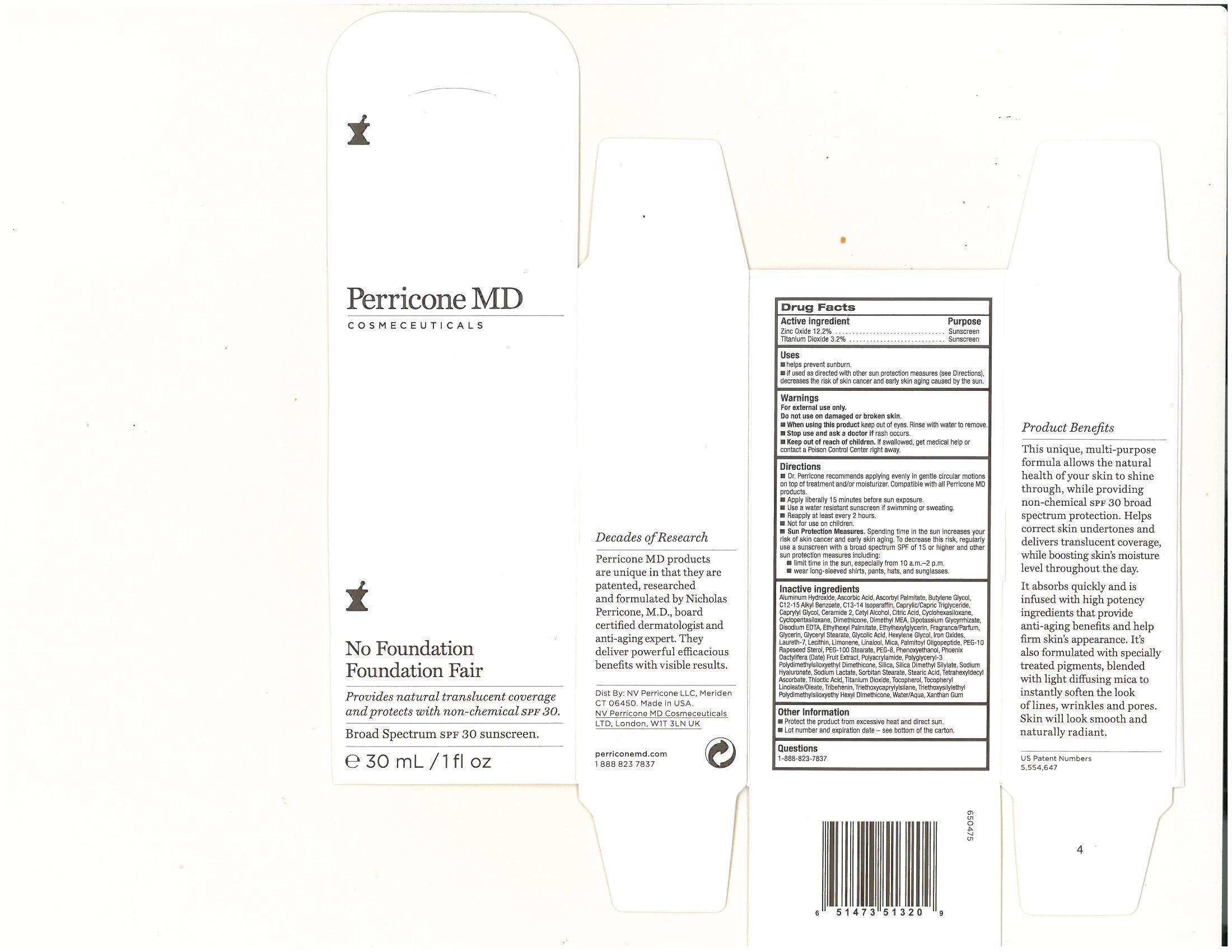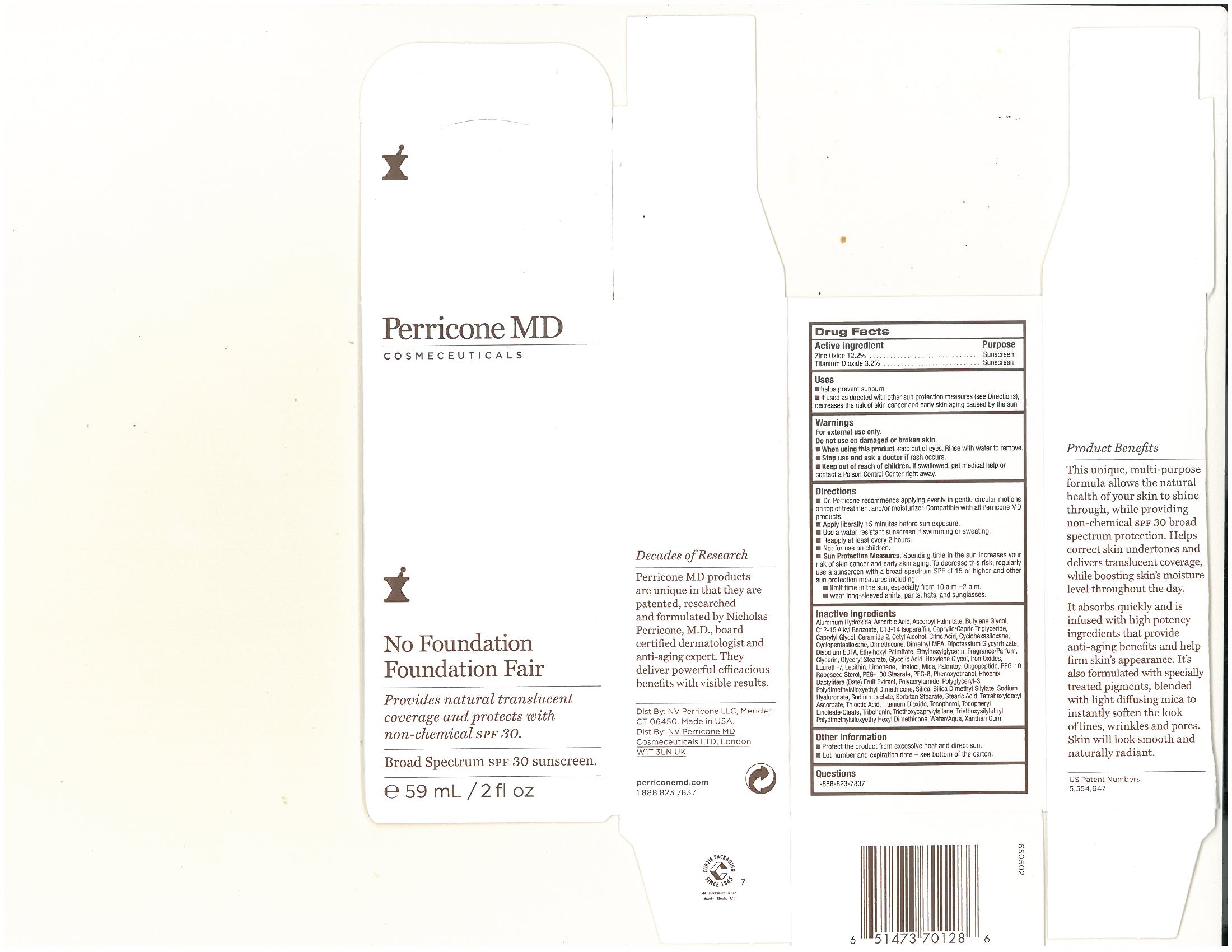 DRUG LABEL: No Foundation Foundation Fair
                
NDC: 62742-4060 | Form: CREAM
Manufacturer: Allure Labs, Inc
Category: otc | Type: HUMAN OTC DRUG LABEL
Date: 20131216

ACTIVE INGREDIENTS: ZINC OXIDE 122 mg/1 mL; TITANIUM DIOXIDE 32 mg/1 mL
INACTIVE INGREDIENTS: ALUMINUM HYDROXIDE; ASCORBIC ACID; ASCORBYL PALMITATE; BUTYLENE GLYCOL; ALKYL (C12-15) BENZOATE; C13-14 ISOPARAFFIN ; MEDIUM-CHAIN TRIGLYCERIDES; CAPRYLYL GLYCOL ; CERAMIDE 2; CETYL ALCOHOL; CITRIC ACID MONOHYDRATE; CYCLOMETHICONE 6; CYCLOMETHICONE 5; DIMETHICONE; DEANOL; GLYCYRRHIZINATE DIPOTASSIUM ; EDETATE DISODIUM; ETHYLHEXYL PALMITATE; ETHYLHEXYLGLYCERIN ; GLYCERIN; GLYCERYL MONOSTEARATE; GLYCOLIC ACID; HEXYLENE GLYCOL; FERRIC OXIDE RED  ; LAURETH-7; LECITHIN, SOYBEAN; MICA; PALMITOYL OLIGOPEPTIDE; PEG-10 RAPESEED STEROL; PEG-100 STEARATE; POLYETHYLENE GLYCOL 400 ; PHENOXYETHANOL; DATE ; POLYACRYLAMIDE (10000 MW) ; SILICON DIOXIDE; HYALURONATE SODIUM; SODIUM LACTATE; SORBITAN MONOSTEARATE; STEARIC ACID; TETRAHEXYLDECYL ASCORBATE; .ALPHA.-LIPOIC ACID; TOCOPHEROL; .ALPHA.-TOCOPHEROL ACETATE; TRIBEHENIN; TRIETHOXYCAPRYLYLSILANE ; WATER; XANTHAN GUM 

DRUG FACTS

ACTIVE INGREDIENTS:
Zinc Oxide - 12.2%
Titanium Dioxide 3.2%

Purpose: Sunscreen

Uses:

Helps prevent sunburn if used as directed with other sun protection measures decreases the risk of skin cancer and early skin aging caused by the sun

Warnings

For External Use Only

Do not use on broken and damaged skin

When using this product keep out of eyes. Rinse with water to remove

Stop use and ask doctor if rash ocuur

Keep out of reach of children. If swallowed, get medical help or contact a Poison Control Center right away

Directions:

- Dr. Perricone recommends applying evenly in gentle circular motions on top of treatment and/or moisturizer. Compatible with all Perricone MD products.
- Apply liberally 15 minutes before sun exposure.
- Use a water resistant sunscreen if swimming or sweating.
- Re apply at least every 2 hours.
- Not for use on children.
- Sun Protection Measures. Spending time in the sun increases your risk of skin cancer and early aging. To decrease this risk regularly use a sunscreen with a broad spectrum SPF of 15 or higher and other sun protection measures including;
  1. Limit time in the sun, especially between 10am to 2pm
- 2. Wear long sleeved shirts, pants, hats, and sun glasses

STORAGE AND HANDLING

Protect the product from excessive heat and direct sun.

INACTIVE INGREDIENT

Aluminum Hydroxide, Accorbic Acid, Ascorbyl Palmitate, Butylene Glycol, C12-C15 Alkyl Benzoate, C13-14 Isoparaffin, Caprylic/Capric Triglyceride, Caprylyl Glycol, Ceramide 2, Cetyl Alcohol, Citric Acid, Cyclohexasiloxane, Cyclopentasiloxane, Dimethicone, Dimethyl MEA, Dipotassium Glycyrrhizate, Disodium EDTA, Ethylhexyl Palmitate, Ethylhexyl Palmitate, Ethylhexylglycerin, Fragrance/Parfum, Glycerin, Glyceryl Stearate, Glycolic Acid, Hexylene Glycol, Iron Oxides, Laureth-7, Lecithin, Limonene, Linalool, Mica, Palmitoyl Oligopeptide, PEG-10 Rapseed Sterol, PEG-100 Stearate, P:EG-8, Phenoxyethanol, Phoenix Dactylifera (Date) Fruit Extract, Polyarylamide, Polyglyceryl-3 Polydimethylsiloxyethyl Dimethicone, Silica, Silica Dimethyl Siylate, Sodium Hyaluronate, Sodium Lactate, Sorbitan Stearate, Stearic Acid, Tetrahexyldecyl Ascorbate, Thiotic Acid, Titanium Dioxide, Tocopheryl, Tocopheryl Linolate/Oleate, Tribehenin, Triethoxycaprylsilane, Triethoxysilyethyl Polydimethylsiloxyethy Hexyl Dimethicone, Water/Aqua, Xanthan Gum

PACKAGE LABEL

Distributed By: NV Perricone LLC, Meriden CT 06450, Made in USA

NV Perricone MD Cosmeceuticals LTD, London. W1T 3LN UK

www.perriconemd.com

1 888 823 7837